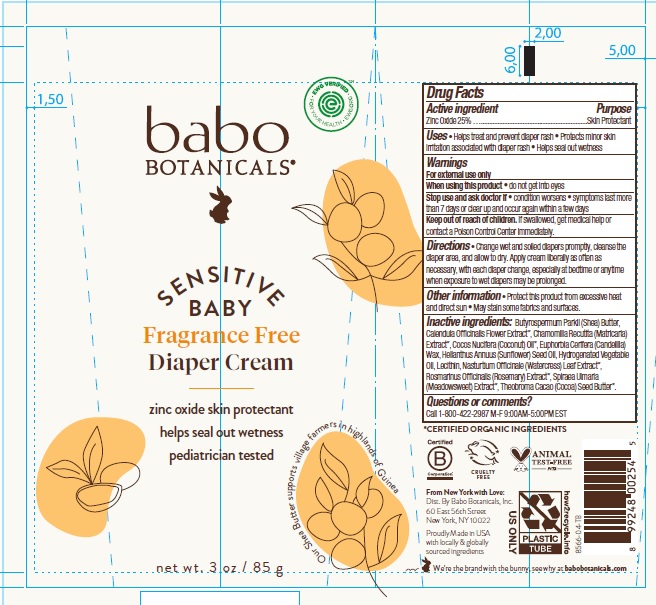 DRUG LABEL: Babo Fragrance Free Diaper Cream
NDC: 79265-8566 | Form: CREAM
Manufacturer: Babo Botanicals, Inc.
Category: otc | Type: HUMAN OTC DRUG LABEL
Date: 20241212

ACTIVE INGREDIENTS: ZINC OXIDE 25 g/100 g
INACTIVE INGREDIENTS: CALENDULA OFFICINALIS FLOWER 0.001 g/100 g; CANDELILLA WAX 5 g/100 g; FILIPENDULA ULMARIA FLOWER 0.001 g/100 g; SHEA BUTTER 5 g/100 g; NASTURTIUM OFFICINALE FLOWERING TOP 0.001 g/100 g; ROSEMARY 0.25 g/100 g; COCOA BUTTER 0.75 g/100 g; CHAMOMILE 0.001 g/100 g; SUNFLOWER OIL 43.744 g/100 g; CORN OIL 10 g/100 g; LECITHIN, SUNFLOWER 0.25 g/100 g; COCONUT OIL 10 g/100 g; GLYCERIN 0.002 g/100 g

Babo Fragrance Free Diaper Cream

Active ingredient

Zinc Oxide 25%

Purpose

Skin Protectant

Uses

- Helps treat and prevent diaper rash
- Protects minor skin irritation associated with diaper rash
- Helps seal out wetness

Warnings

For external use only.

When using this product

- do not get into eyes

Stop use and ask a doctor if

- condition worsens
- symptoms last more than 7 days or clear up and occur again within a few days

Keep out of reach of children.

If swallowed, get medical help or contact a Poison Control Center immediately.

Directions

- Change wet and soiled diapers promptly, cleanse the diaper area, and allow to dry. Apply cream liberally as often as necessary, with each diaper change, especially at bedtime or anytime when exposure to wet diapers may be prolonged.

Other information

- Protect this product from excessive heat and direct sun.
- May stain some fabrics and surfaces.

Inactive ingredients

BUTYROSPERMUM PARKII (SHEA) BUTTER, CALENDULA OFFICINALIS FLOWER EXTRACT*, CHAMOMILLA RECUTITA (MATRICARIA) EXTRACT*, COCOS NUCIFERA (COCONUT) OIL*, EUPHORBIA CERIFERA (CANDELILLA) WAX, HELIANTHUS ANNUUS (SUNFLOWER) SEED OIL, HYDROGENATED VEGETABLE OIL, LECITHIN, NASTURTIUM OFFICINALE (WATERCRESS) LEAF EXTRACT*, ROSMARINUS OFFICINALIS (ROSEMARY) EXTRACT*, SPIRAEA ULMARIA (MEADOWSWEET) EXTRACT*, THEOBROMA CACAO (COCOA) SEED BUTTER*

*Certified Organic Ingredients

Questions or comments?

Call 1-800-422-2987 M-F 9:00AM-5:00PM EST